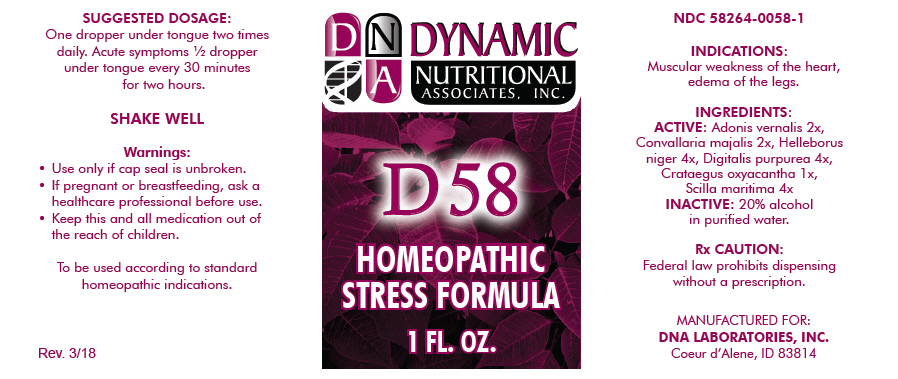 DRUG LABEL: D-58
NDC: 58264-0058 | Form: SOLUTION
Manufacturer: DNA Labs, Inc.
Category: homeopathic | Type: HUMAN OTC DRUG LABEL
Date: 20250113

ACTIVE INGREDIENTS: ADONIS VERNALIS 2 [hp_X]/1 mL; CONVALLARIA MAJALIS 2 [hp_X]/1 mL; HELLEBORUS NIGER ROOT 4 [hp_X]/1 mL; DIGITALIS 4 [hp_X]/1 mL; CRATAEGUS LAEVIGATA FRUIT 1 [hp_X]/1 mL; DRIMIA MARITIMA BULB 4 [hp_X]/1 mL
INACTIVE INGREDIENTS: ALCOHOL; WATER

D-58

NDC 58264-0058-1

INDICATIONS

PURPOSE

Muscular weakness of the heart, edema of the legs.

INGREDIENTS

ACTIVE

Adonis vernalis 2x, Convallaria majalis 2x, Helleborus niger 4x, Digitalis purpurea 4x, Crataegus oxyacantha 1x, Scilla maritima 4x

INACTIVE

20% alcohol in purified water.

Rx CAUTION

Federal law prohibits dispensing without a prescription.

SUGGESTED DOSAGE

One dropper under tongue two times daily. Acute symptoms ½ dropper under tongue every 30 minutes for two hours.

STORAGE AND HANDLING

SHAKE WELL

Warnings

- Use only if cap seal is unbroken.

PREGNANCY OR BREAST FEEDING

- If pregnant or breastfeeding, ask a healthcare professional before use.

KEEP OUT OF REACH OF CHILDREN

- Keep this and all medication out of the reach of children.

To be used according to standard homeopathic indications.

PRINCIPAL DISPLAY PANEL - 1 FL. OZ. Bottle Label

DYNAMIC
NUTRITIONAL
ASSOCIATES, INC.

D 58

HOMEOPATHIC
STRESS FORMULA

1 FL. OZ.